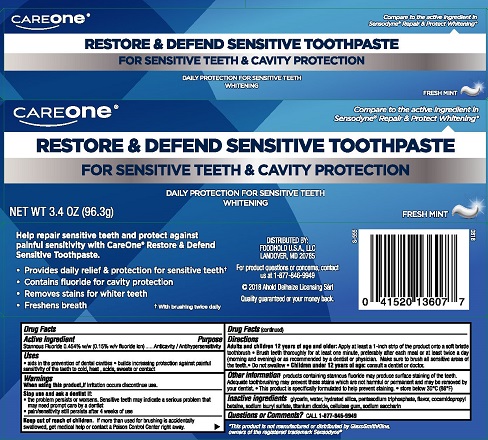 DRUG LABEL: Care One Restore and Defend
NDC: 41520-722 | Form: PASTE, DENTIFRICE
Manufacturer: Foodhold U.S.A.
Category: otc | Type: HUMAN OTC DRUG LABEL
Date: 20251112

ACTIVE INGREDIENTS: STANNOUS FLUORIDE 0.15 g/100 g
INACTIVE INGREDIENTS: GLYCERIN; SACCHARIN SODIUM; WATER; TITANIUM DIOXIDE; SODIUM TRIPOLYPHOSPHATE ANHYDROUS; CARBOXYMETHYLCELLULOSE SODIUM, UNSPECIFIED FORM; COCAMIDOPROPYL BETAINE; SODIUM LAURYL SULFATE; HYDRATED SILICA

5820293 Care One Restore & Defend Sensitive Whitening Toothpaste

Drug Facts

Active ingredient

Stannous Fluoride 0.454% w/w (0.15% fluoride ion)

Purpose

Anticavity/Antihypersensitivity

Uses

- aids in the prevention of dental cavities
- builds increasing protection against painful sensitivity of the teeth to cold, heat, acids, sweets or contact

Warnings

When using this product, if irritation occurs discontinue use.

Stop use and ask a dentist if:

- the problem persists or worsens. Sensitive teeth may indicate a serious problem that may need prompt care by a dentist.
- pain/sensitivity still persists after 4 weeks of use

Keep out of reach of children. If more than used for brushing is accidentally swallowed get medical help or contact a poison control center right away.

Directions

Adults and children 12 years of age and older: Apply at least a 1-inch strip of the product onto a soft bristle toothbrush.

- Brush teeth thoroughly for at least one minute, preferably after each meal or at least twice a day (morning and evening) or as directed by a dentist or physician. Make sure to brush all sensitive areas of the teeth.
- Do not swallow
- Children under 12 years of age: consult a dentist or doctor

Other information

products containing stannous fluoride may produce surface staining of the teeth. Adequate toothbrushing may prevent these stains which are not harmful or permanent and may be removed by your dentist.

This product is specifically formulated to help prevent staining.

- store below 30°C (86°F)

INACTIVE INGREDIENT

Inactive ingredients glycerin, water, hydrated silica, pentasodium triphosphate, flavor, cocamidopropyl betaine, sodium lauryl sulfate, titanium dioxide, cellulose gum, sodium saccharin

Questions or Comments? CALL 1-877-846-9949

DISTRIBUTED BY:

FOODHOLD U.S.A., LLC

LANDOVER, MD 20785

For product questions or concerns, contact us at 1-877-849-9949

PACKAGE LABEL

CareOne®

RESTORE & DEFEND SENSITIVE TOOTHPASTE

FOR SENSITIVE TEETH & CAVITY PROTECTION

DAILY PROTECTION FOR SENSITIVE TEETH

WHITENING

FRESH MINT

NET WT 3.4 OZ (96.3 g)